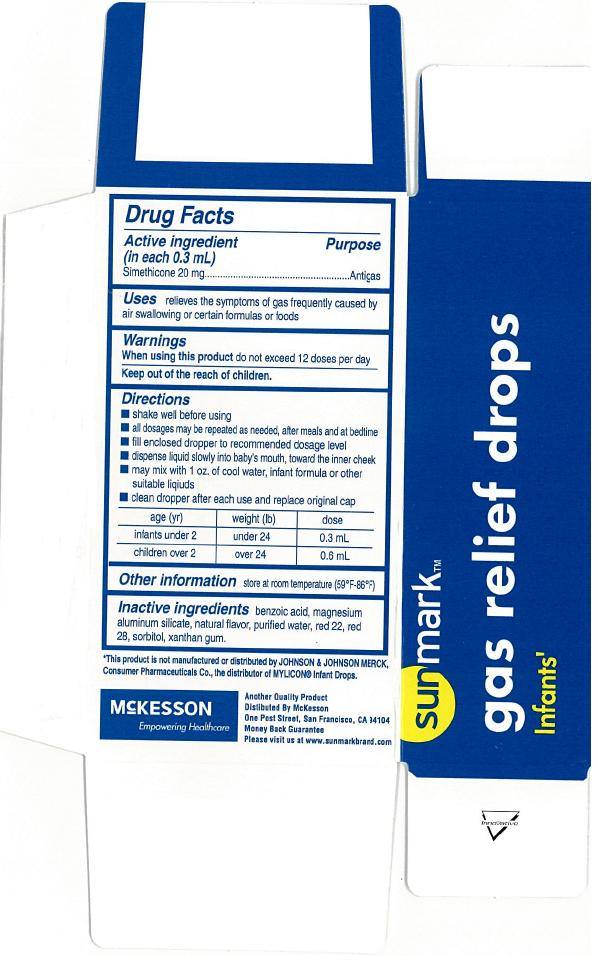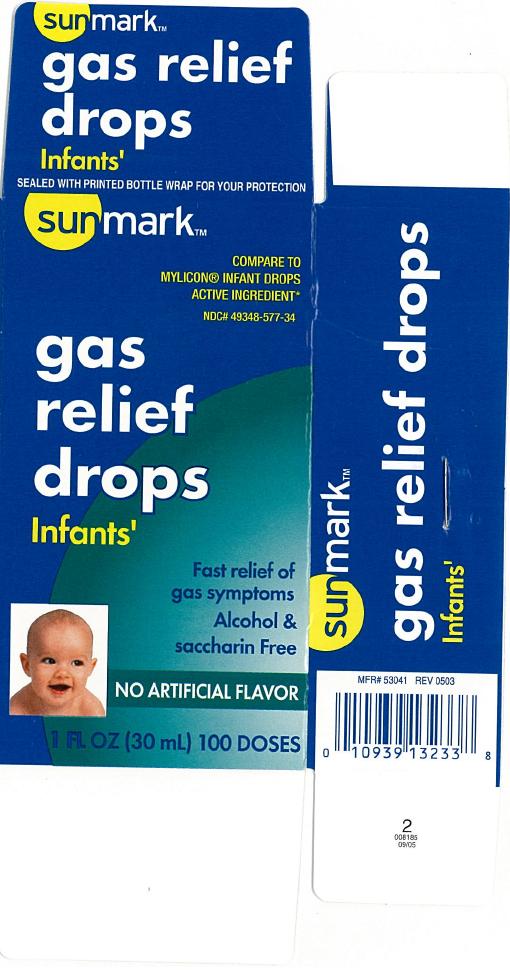 DRUG LABEL: Sunmark infants gas relief drops
NDC: 49348-577 | Form: EMULSION
Manufacturer: McKesson
Category: otc | Type: HUMAN OTC DRUG LABEL
Date: 20120910

ACTIVE INGREDIENTS: DIMETHICONE 20 mg/0.3 mL
INACTIVE INGREDIENTS: BENZOIC ACID; MAGNESIUM ALUMINUM SILICATE; WATER; D&C RED NO. 22; D&C RED NO. 28; SORBITOL; XANTHAN GUM

Sunmark gas relief drops infants

Active ingredient (in each 0.3 mL)

Simethicone 20 mg

Purpose

Antigas

Uses

relieves the symptoms of gas frequently caused by air swallowing or certain formulas or foods

Warnings

When using this product

do not exceed 12 doses per day

Directions

- shake well before using
- all dosages may be repeated as needed, after meals and at bedtime
- fill enclosed dropper to recommended dosage level
- dispense liquid slowly into baby's mouth, toward the inner cheek
- may mix with 1 oz. of cool water, infant formula or other suitable liquids
- clean dropper after each use replace original cap.
  age (yr) | weight (lb) | dose
  infants under 2 | under 24 | 0.3 mL
  children over 2 | over 24 | 0.6 mL

Other information

store at room temperature (59oF-86oF)

Inactive ingredients

benzoic acid, red # 22, red # 28, flavor, magnesium aluminum silicate, purified water, sorbitol, xanthan gum.

Principal Display Panel

Sunmark

compare to Mylicon® Infant drops active ingredient

gas relief drops infants'

Fast relief of gas symptoms

Alcohol and Saccharin free

No artificial flavor

1 fl oz (30 mL) 100 Doses